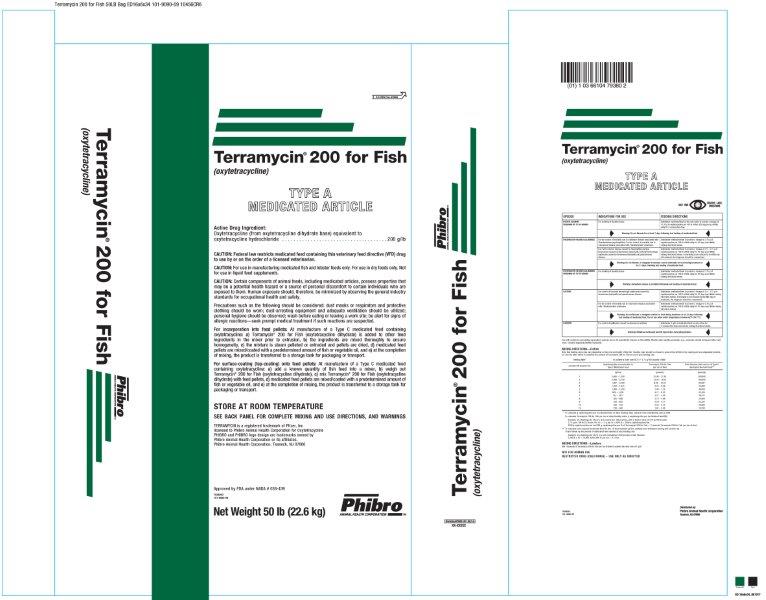 DRUG LABEL: Terramycin 200 for Fish
NDC: 66104-7938 | Form: POWDER
Manufacturer: Phibro Animal Health
Category: animal | Type: VFD TYPE A MEDICATED ARTICLE ANIMAL DRUG LABEL
Date: 20231106

ACTIVE INGREDIENTS: OXYTETRACYCLINE HYDROCHLORIDE 200 g/0.45 kg
INACTIVE INGREDIENTS: SOYBEAN OIL; RICE BRAN

Terramycin® 200 for Fish
TYPE A MEDICATED ARTICLE

Active Drug Ingredient:

Oxytetracycline (from oxytetracycline dihydrate) equivalent to

oxytetracycline hydrochloride (Terramycin®) . . . . . . . . . . . . . . . . . . . . . 200 g/lb

CAUTION:

CAUTION: Federal law restricts medicated feed containing this veterinary feed directive (VFD) drug to use by or on the order of a licensed veterinarian.

CAUTION: For use in manufacturing medicated fish and lobster feeds only. For use in dry feeds only. Not for use in liquid feed supplements.

CAUTION: Certain components of animal feeds, including medicated premixes, possess properties that may be a potential health hazard or a source of personal discomfort to certain individuals who are exposed to them. Human exposure should, therefore, be minimized by observing the general industry standards for occupational health and safety.

Precautions such as the following should be considered: dust masks or respirators and protective clothing should be worn; dust-arresting equipment and adequate ventilation should be utilized; personal hygiene should be observed; wash before eating or leaving a work site; be alert for signs of allergic reactions—seek prompt medical treatment if such reactions are suspected.

STORE AT ROOM TEMPERATURE

SEE BACK PANEL FOR COMPLETE MIXING AND USE DIRECTIONS, AND WARNINGS

Terramycin is a registered trademark of Pfizer, Inc.,

licensed to Phibro Animal Health Corporation, for Oxytetracycline.

PHIBRO and PHIBRO logo design are trademarks owned by

Phibro Animal Health Corporation or its affiliates

Phibro Animal Health Corporation, Teaneck, NJ 07666

Net Weight 50 lb (22.6 kg)

Approved by FDA under NADA #038-439

7938000

101-9090-09

DOSAGE AND ADMINISTRATION

SPECIES | INDICATIONS FOR USE | FEEDING DIRECTIONS
SALMONIDS | For control of ulcer disease caused by Hemophilus piscium, furunculosis caused by Aeromonas salmonicida, bacterial hemorrhagic septicemia caused by Aeromonas liquefaciens and pseudomonas disease. | Administer medicated feed to provide a dosage of 2.5 - 3.75 g of oxytetracycline per 100 lb of fish daily for 10 days (see finfish mixing directions below). If mortality is not reduced by the fifth day; of treatment, the diagnosis should be reexamined.
 | Warning: Do not liberate or slaughter salmonids for food during treatment or for 21 days following last feeding of medicated feed.
PACIFIC SALMON; WEIGHING UP TO 30 GRAMS | For marking of skeletal tissue. | Administer medicated feed as the sole ration to provide a dosage of 11.35 g of oxytetracycline per 100 lb of fish (250 mg per kg of fish) daily for 4 consecutive days.
 | Warning: Do not liberate for at least 7 days following last feeding of medicated feed.
FRESHWATER-REARED; SALMONIDS | For the control of mortality in freshwater-reared salmonids due to coldwater disease associated with Flavobacterium psychrophilum. | Administer medicated feed to provide a dosage of 3.75 g of oxytetracycline per 100 lb of fish daily for 10 days (see finfish mixing directions below).
 | Warning: Do not liberate or slaughter freshwater-reared salmonids for food during treatment or for 21 days following last feeding of medicated feed.
FRESHWATER-REARED SALMONIDS WEIGHING UP TO 55 GRAMS | For marking of skeletal tissue. | Administer medicated feed to provide a dosage of 3.75 g of oxytetracycline per 100 lb of fish daily for 10 days (see finfish mixing directions below).
 | Warning: Immediate release is permitted following last feeding of medicated feed.
FRESHWATER-REARED; Oncorhynchus mykiss | For the control of mortality in freshwater-reared Oncorhynchus mykiss due to columnaris disease associated with Flavobacterium columnare. | Administer medicated feed to provide a dosage of 3.75 g of oxytetracycline per 100 lb of fish daily for 10 days (see finfish mixing directions below).
 | Warning: Do not liberate or slaughter Oncorhynchus mykissfor food during treatment or for 21 days following last feeding of medicated feed.
CATFISH | For control of bacterial hemorrhagic septicemia caused by Aeromonas liquefaciens and pseudomonas disease. | Administer medicated feed to provide a dosage of 2.5 - 3.75 g of oxytetracycline per 100 lb of fish daily for 10 days (see finfish mixing directions below). If mortality is not reduced by the fifth day of treatment, the diagnosis should be reexamined.
 | Warning: Do not liberate or slaughter catfish for food during treatment or for 21 days following last feeding of medicated feed. Do not use when water temperature is below 62°F (16.7°C).
LOBSTER | For control of gaffkemia caused by Aerococcus viridans. | Administer 1 g/lb of medicated feed as sole ration for 5 consecutive days (see lobster mixing directions below).
 | Warning: Withdraw medicated feed 30 days before harvesting lobsters.

MIXING DIRECTIONS—Finfish

Note that feeding rates may vary depending on the size and health of the fish. Feeding rates should be chosen to ensure that all fish in the rearing unit are adequately medicated.

Use the table below to calculate the amount of Terramycin 200 for Fish to use at your feeding rate.

Feeding Rate* | To achieve a dose rate of 2.5 – 3.75 g/100 pounds of fish
pounds/100 pounds (%) | Terramycin concentration Type C Medicated Feed | Terramycin 200 for Fish per ton of feed | Total biomass that one ton of medicated feed will treat**
1; 2; 3; 4; 5; 6; 7; 8; 9; 10; 15 | (g/ton); 5,000 – 7,500; 2,500 – 3,750; 1,667 – 2,500; 1,250 – 1,875; 1,000 – 1,500; 833 – 1,250; 714 – 1071; 625 – 938; 556 – 833; 500 – 750; 333 – 500 | (pounds); 25.00 – 37.50; 12.50 – 18.75; 8.33 – 12.50; 6.25 – 9.38; 5.00 – 7.50; 4.17 – 6.25; 3.57 – 5.36; 3.13 – 4.69; 2.78 – 4.17; 2.50 – 3.75; 1.67 – 2.50 | (pounds); 200,000; 100,000; 66,667; 50,000; 40,000; 33,333; 28,571; 25,000; 22,222; 20,000; 13,333

* To calculate g Terramycin per ton finished feed at other feeding rates: (desired dose rate/feeding rate) x 2000

To calculate Terramycin 200 for Fish per ton at other feeding rates: g Terramycin per ton finished feed/200

Example: at a feeding rate of 2.5% (2.5 pounds per 100 pounds), with a desired dose of 3.75 g/100 pounds: 3.75 g per 100 lb/2.5 lb per 100 lb = 1.5 g per lb x 2000 lb = 3000 g Terramycin/ton

3000 g Terramycin per ton/200 g Terramycin per lb of Terramycin 200 for Fish = 15 pounds Terramycin per ton of feed

** To calculate total required medicated feed for the 10 day treatment period, multiply total estimated rearing unit biomass by 10 and divide by the pounds of medicated feed needed at your feeding rate

Example: at a feeding rate of 2% in a unit containing 5,000 pounds of fish biomass:

5,000 lb x 10 = 50,000 lb/100,000 lb per ton = 0.5 tons

MIXING DIRECTIONS—Lobsters

Mix 10 pounds of Terramycin 200 for Fish per ton of feed to achieve the dose rate of 1 g/lb.

INDICATIONS AND USAGE

NOT FOR HUMAN USE

RESTRICTED DRUG (CALIFORNIA) – USE ONLY AS DIRECTED

Terramycin 200 for Fish